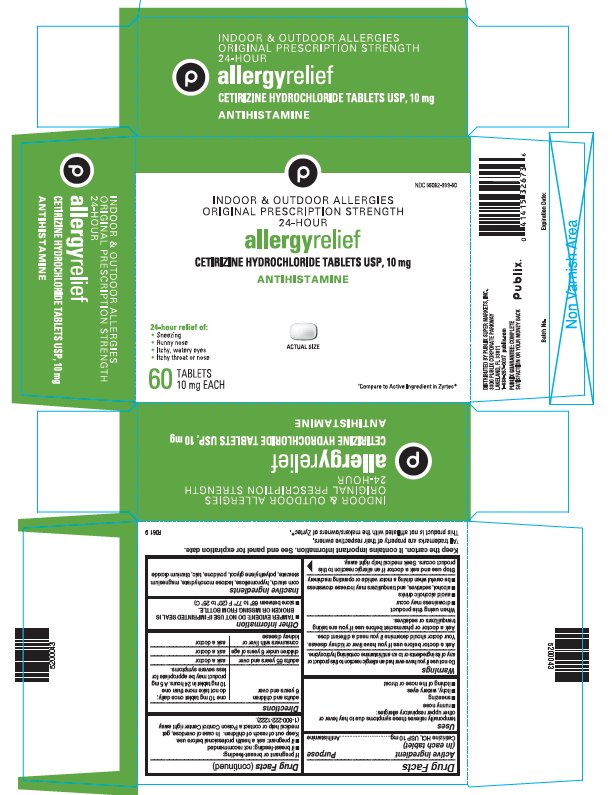 DRUG LABEL: Cetirizine Hydrochloride
NDC: 56062-939 | Form: TABLET
Manufacturer: Publix Super Markets Inc
Category: otc | Type: HUMAN OTC DRUG LABEL
Date: 20190819

ACTIVE INGREDIENTS: CETIRIZINE HYDROCHLORIDE 10 mg/1 1
INACTIVE INGREDIENTS: STARCH, CORN; HYPROMELLOSE, UNSPECIFIED; LACTOSE MONOHYDRATE; MAGNESIUM STEARATE; POLYETHYLENE GLYCOL, UNSPECIFIED; POVIDONE, UNSPECIFIED; TALC; TITANIUM DIOXIDE

Drug Facts

ACTIVE INGREDIENT (IN EACH TABLET)

Cetirizine HCl, USP 10 mg

PURPOSE

Antihistamine

USES

Temporarily relieves these symptoms due to hay fever or other upper respiratory allergies:

- runny nose
- sneezing
- itchy, watery eyes
- itching of the nose or throat

WARNINGS

Do not use

If you have ever had an allergic reaction to this product or any of its ingredients or to an antihistamine containing hydroxyzine.

Ask a doctor before use if you have

Liver or kidney disease. Your doctor should determine if you need a different dose.

Ask a doctor or pharmacist before use if you are

Taking tranquilizers or sedatives.

When using this product

- drowsiness may occur
- avoid alcoholic drinks
- alcohol, sedatives, and tranquilizers may increase drowsiness
- be careful when driving a motor vehicle or operating machinery

Stop use and ask a doctor if

An allergic reaction to this product occurs. Seek medical help right away.

If pregnant or breast-feeding

- if breast-feeding: not recommended
- if pregnant: ask a health professional before use.

Keep out of reach of children.

In case of overdose, get medical help or contact a Poison Control Center right away (1-800-222-1222).

DIRECTIONS

adults and children 6 years and over | one 10 mg tablet once daily; do not take more than one 10 mg tablet in 24 hours. A 5 mg product may be appropriate for less severe symptoms.
adults 65 years and over | ask a doctor
children under 6 years of age | ask a doctor
consumers with liver or kidney disease | ask a doctor

Other information

- TAMPER EVIDENT: DO NOT USE IF IMPRINTED SEAL IS BROKEN OR MISSING FROM BOTTLE.
- store between 68° to 77° F (20° to 25° C)

INACTIVE INGREDIENTS

Corn starch, hypromellose, lactose monohydrate, magnesium stearate, polyethylene glycol, povidone, talc, titanium dioxide

PRINCIPAL DISPLAY PANEL - 10 mg Tablet Bottle Carton

NDC 56062-939-60

INDOOR & OUTDOOR ALLERGIES
ORIGINAL PRESCRIPTION STRENGTH
24-HOUR

allergyrelief

CETIRIZINE HYDROCHLORIDE TABLETS USP, 10 mg

ANTIHISTAMINE

24-hour relief of:

- Sneezing
- Runny nose
- Itchy, watery eyes
- Itchy throat or nose

ACTUAL SIZE

60
TABLETS
10 mg EACH

†Compare to Active Ingredient in Zyrtec®